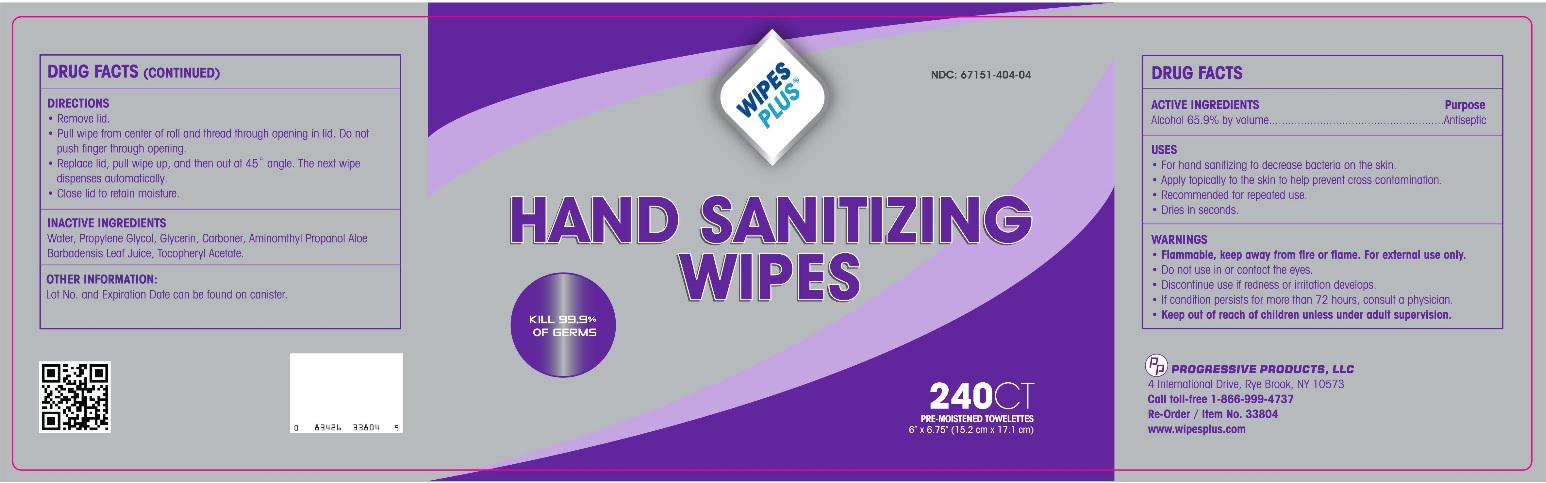 DRUG LABEL: Alcohol
NDC: 67151-404 | Form: SWAB
Manufacturer: Progressive Products, LLC
Category: otc | Type: HUMAN OTC DRUG LABEL
Date: 20211227

ACTIVE INGREDIENTS: ALCOHOL 1.31 g/1 1
INACTIVE INGREDIENTS: WATER; PROPYLENE GLYCOL; GLYCERIN; CARBOMER HOMOPOLYMER TYPE C; AMINOMETHYLPROPANOL; ALOE VERA LEAF; .ALPHA.-TOCOPHEROL ACETATE

Drug Facts

ACTIVE INGREDIENTS

Alcohol 65.9% by volume

PURPOSE

Antiseptic

USES

- For hand sanitizing to decrease the bacteria on the skin.
- Apply topically to the skin to help prevent cross contamination
- Recommended for repeated use.
- Dries in seconds.

WARNINGS

- Flammable, keep away from fire or flame.
- For external use only.

OTC - DO NOT USE SECTION

Do not use in or contact the eyes

OTC - STOP USE SECTION

Discontinue use if irritation and redness develop. If condition persists for more than 72 hours, consult a physician.

OTC - KEEP OUT OF REACH OF CHILDREN SECTION

Keep out of reach of children unless under adult supervision.

OTHER WARNINGS

If swallowed, get medical help or contact a poison Control Center immediately.

DIRECTIONS

- Remove lid.
- Pull wipe from center of the roll and thread through opening in lid. Do not push finger through the opening.
- Replace lid, pull wipe up, and than out at a 45th angle. The next wipe dispenses automatically.
- Close lid to retain moisture.

OTHER INFORMATION

Lot No. and Expiration Date can be found on the canister.

INACTIVE INGREDIENTS

Water, Propylene Glycol, Glycerin, Carbomer, Aminomethyl Propanol, Aloe Barbadensis Leaf Juice, Tocopheryl Acetate.

PRINCIPAL DISPLAY PANEL

NDC 67151-404-04

WIPES PLUS ®

HAND SANITIZING WIPES

KILLS 99.9% OF GERMS

240 CT

PRE-MOISTENED TOWELETTES

6" X 6.75" (15.2 cm X 17.1 cm)